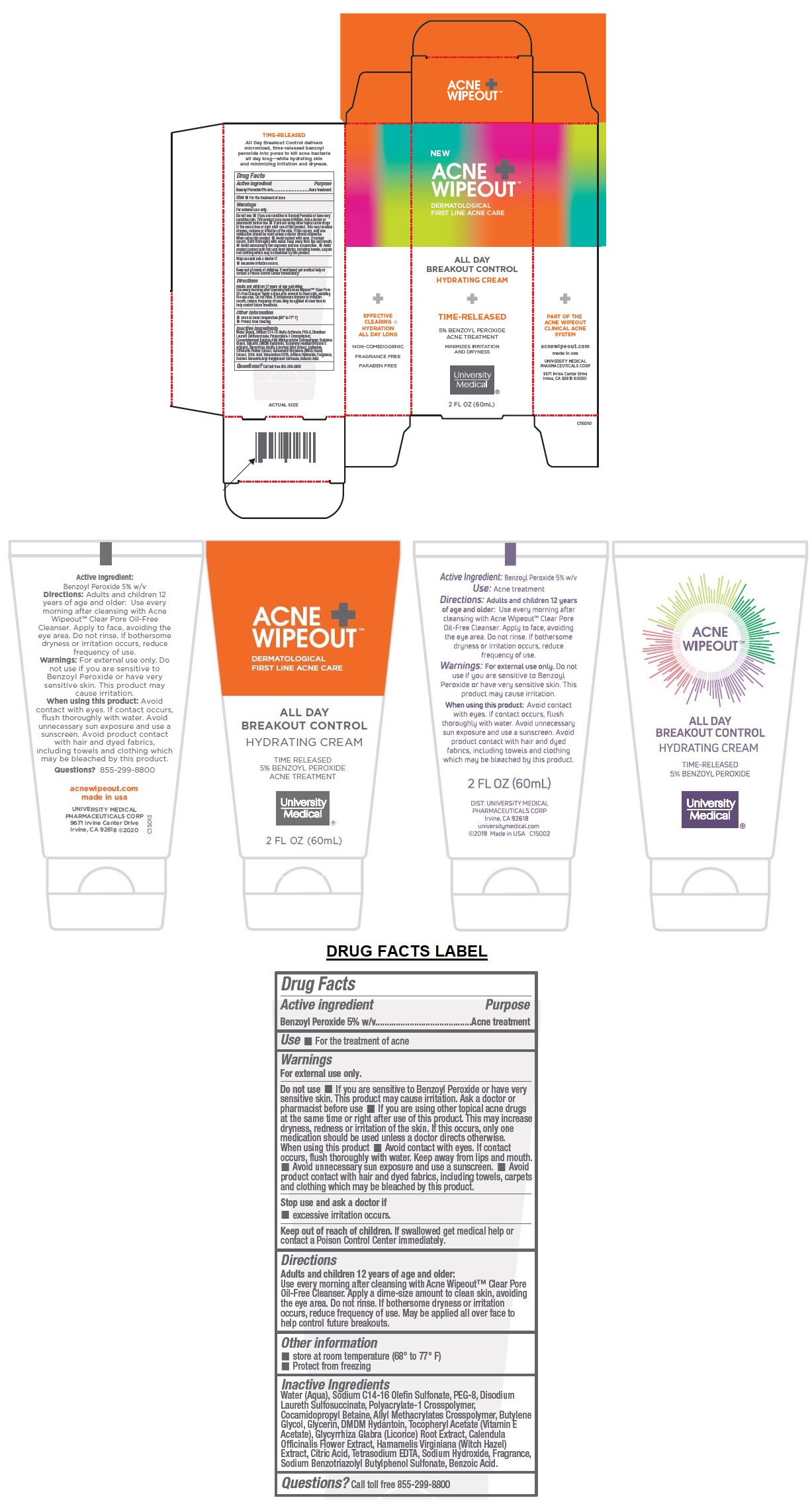 DRUG LABEL: ACNE WIPEOUT ALL DAY BREAKOUT CONTROL
NDC: 50544-152 | Form: CREAM
Manufacturer: University Medical Pharmaceuticals Corp.
Category: otc | Type: HUMAN OTC DRUG LABEL
Date: 20201002

ACTIVE INGREDIENTS: BENZOYL PEROXIDE 5 g/100 mL
INACTIVE INGREDIENTS: WATER; SODIUM C14-16 OLEFIN SULFONATE; POLYETHYLENE GLYCOL 400; DISODIUM LAURETH SULFOSUCCINATE; CARBOMER HOMOPOLYMER, UNSPECIFIED TYPE; COCAMIDOPROPYL BETAINE; ALLYL METHACRYLATE/GLYCOL DIMETHACRYLATE CROSSPOLYMER; BUTYLENE GLYCOL; GLYCERIN; DMDM HYDANTOIN; .ALPHA.-TOCOPHEROL ACETATE; GLYCYRRHIZA GLABRA; CALENDULA OFFICINALIS FLOWER; HAMAMELIS VIRGINIANA TOP; CITRIC ACID MONOHYDRATE; EDETATE SODIUM; SODIUM HYDROXIDE; SODIUM BENZOTRIAZOLYL BUTYLPHENOL SULFONATE; BENZOIC ACID

ACNE WIPEOUT™ ALL DAY BREAKOUT CONTROL

Active ingredient

Benzoyl Peroxide 5% w/v

Purpose

Acne treatment

Use

• For the treatment of acne

Warnings

For external use only.

Do not use • If you are sensitive to Benzoyl Peroxide or have very sensitive skin. This product may cause irritation. Ask a doctor or pharmacist before use • If you are using other topical acne drugs at the same time or right after use of this product. This may increase dryness, redness or irritation of the skin. If this occurs, only one medication should be used unless a doctor directs otherwise.
When using this product • Avoid contact with eyes. If contact occurs, flush thoroughly with water. Keep away from lips and mouth. • Avoid unnecessary sun exposure and use a sunscreen. • Avoid product contact with hair and dyed fabrics, including towels, carpets and clothing which may be bleached by this product.

Stop use and ask a doctor if
• excessive irritation occurs.

Keep out of reach of children. If swallowed get medical help or contact a Poison Control Center immediately.

Directions

Adults and children 12 years of age and older:
Use every morning after cleansing with Acne Wipeout™ Clear Pore Oil-Free Cleanser. Apply a dime-size amount to clean skin, avoiding the eye area. Do not rinse. If bothersome dryness or irritation occurs, reduce frequency of use. May be applied all over face to help control future breakouts.

Other information

- store at room temperature (68° to 77° F)
- Protect from freezing

Inactive Ingredients

Water (Aqua), Sodium C14-16 Olefin Sulfonate, PEG-8, Disodium Laureth Sulfosuccinate, Polyacrylate-1 Crosspolymer, Cocamidopropyl Betaine, Allyl Methacrylates Crosspolymer, Butylene Glycol, Glycerin, DMDM Hydantoin, Tocopheryl Acetate (Vitamin E Acetate), Glycyrrhiza Glabra (Licorice) Root Extract, Calendula Officinalis Flower Extract, Hamamelis Virginiana (Witch Hazel) Extract, Citric Acid, Tetrasodium EDTA, Sodium Hydroxide, Fragrance, Sodium Benzotriazolyl Butylphenol Sulfonate, Benzoic Acid.

Questions? call toll free 855-299-8800

DERMATOLOGICAL FIRST LINE ACNE CARE

HYDRATING CREAM

TIME-RELEASED

5% BENZOYL PEROXIDE ACNE TREATMENT

MINIMIZES IRRITATION AND DRYNESS

PART OF THE ACNE WIPEOUT CLINICAL ACNE SYSTEM

acnewipeout.com

made in usa

UNIVERSITY MEDICAL

PHARMACEUTICALS CORP

9671 Irvine Center Drive

Irvine, CA 92618 ©2020

EFFECTIVE CLEARING + HYDRATION ALL DAY LONG

NON-COMEDOGENIC

FRAGRANCE FREE

PARABEN FREE

All Day Breakout Control delivers micronized, time-released benzoyl peroxide into pores to kill acne bacteria all day long—while hydrating skin and minimizing irritation and dryness.